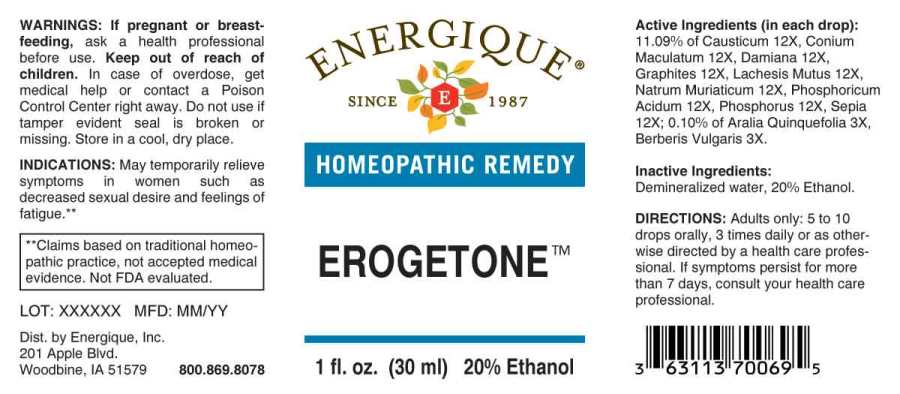 DRUG LABEL: Erogetone
NDC: 44911-0552 | Form: LIQUID
Manufacturer: Energique, Inc.
Category: homeopathic | Type: HUMAN OTC DRUG LABEL
Date: 20220628

ACTIVE INGREDIENTS: AMERICAN GINSENG 3 [hp_X]/1 mL; BERBERIS VULGARIS ROOT BARK 3 [hp_X]/1 mL; CAUSTICUM 12 [hp_X]/1 mL; CONIUM MACULATUM FLOWERING TOP 12 [hp_X]/1 mL; TURNERA DIFFUSA LEAFY TWIG 12 [hp_X]/1 mL; GRAPHITE 12 [hp_X]/1 mL; LACHESIS MUTA VENOM 12 [hp_X]/1 mL; SODIUM CHLORIDE 12 [hp_X]/1 mL; PHOSPHORIC ACID 12 [hp_X]/1 mL; PHOSPHORUS 12 [hp_X]/1 mL; SEPIA OFFICINALIS JUICE 12 [hp_X]/1 mL
INACTIVE INGREDIENTS: WATER; ALCOHOL

Drug Facts:

ACTIVE INGREDIENTS:

(in each drop): 11.09% of Causticum 12X, Conium Maculatum 12X, Damiana 12X, Graphites 12X, Lachesis Mutus 12X, Natrum Muriaticum 12X, Phosphoricum Acidum 12X, Phosphorus 12X, Sepia 12X; 0.10% of Aralia Quinquefolia 3X, Berberis Vulgaris 3X.

INDICATIONS:

May temporarily relieve symptoms in women such as decreased sexal desire and feelings of fatigue.**

**Claims based on traditional homeopathic practice, not accepted medical evidence. Not FDA evaluated.

WARNINGS:

If pregnant or breastfeeding, ask a health professional before use.

Keep out of reach of children. In case of overdose, get medical help or contact a Poison Control Center right away.

Do not use if tamper evident seal is broken or missing.

Store in a cool, dry place.

Keep out of reach of children. In case of overdose, get medical help or contact a Poison Control Center right away.

DIRECTIONS:

Adults only: 5 to 10 drops orally, 3 times daily or as otherwise directed by a health care professional. If symptoms persist for more than 7 days, consult your health care professional.

INDICATIONS:

May temporarily relieve symptoms in women such as decreased sexal desire and feelings of fatigue.**

**Claims based on traditional homeopathic practice, not accepted medical evidence. Not FDA evaluated.

INACTIVE INGREDIENTS:

Demineralized water, 20% Ethanol.

QUESTIONS:

Dist. by Energique, Inc.

201 Apple Blvd.

Woodbine, IA 51579 800.869.8078

PACKAGE LABEL DISPLAY:

ENERGIQUE
SINCE 1987
HOMEOPATHIC REMEDY
EROGETONE
1 fl. oz. (30 ml)